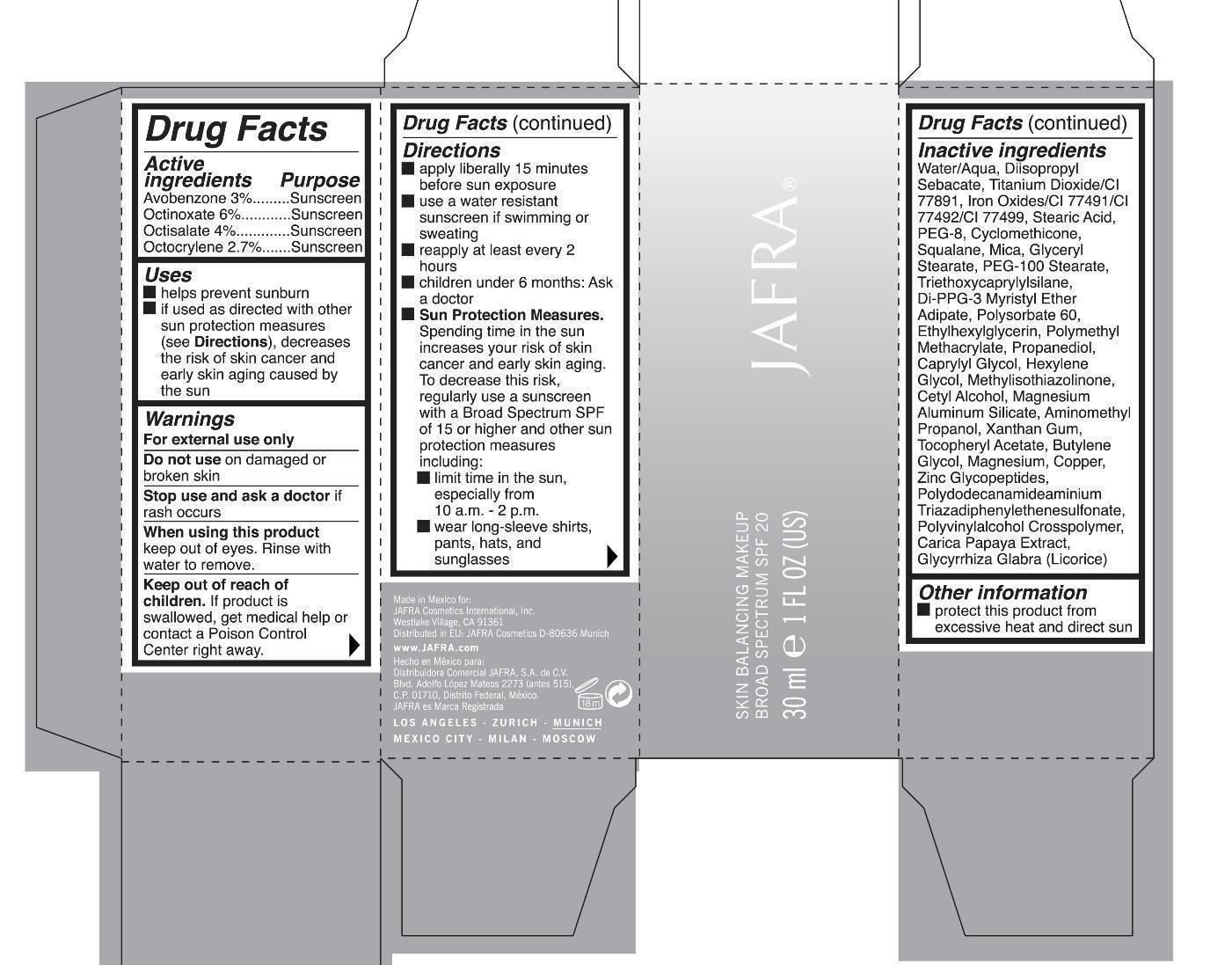 DRUG LABEL: Skin Balancing Makeup Broad Spectrum SPF 20
NDC: 68828-194 | Form: CREAM
Manufacturer: Jafra Cosmetics
Category: otc | Type: HUMAN OTC DRUG LABEL
Date: 20190613

ACTIVE INGREDIENTS: AVOBENZONE 3 g/100 mL; OCTINOXATE 6 g/100 mL; OCTISALATE 4 g/100 mL; OCTOCRYLENE 2.7 g/100 mL
INACTIVE INGREDIENTS: WATER; DIISOPROPYL SEBACATE; TITANIUM DIOXIDE; FERRIC OXIDE RED; FERRIC OXIDE YELLOW; FERROSOFERRIC OXIDE; STEARIC ACID; POLYETHYLENE GLYCOL 400; CYCLOMETHICONE; SQUALANE; MICA; GLYCERYL MONOSTEARATE; PEG-100 STEARATE; TRIETHOXYCAPRYLYLSILANE; DI-PPG-3 MYRISTYL ETHER ADIPATE; POLYSORBATE 60; ETHYLHEXYLGLYCERIN; POLY(METHYL METHACRYLATE; 450000 MW); PROPANEDIOL; CAPRYLYL GLYCOL; HEXYLENE GLYCOL; METHYLISOTHIAZOLINONE; CETYL ALCOHOL; MAGNESIUM ALUMINUM SILICATE; AMINOMETHYLPROPANOL; XANTHAN GUM; .ALPHA.-TOCOPHEROL ACETATE; BUTYLENE GLYCOL; MAGNESIUM; COPPER; PAPAYA; GLYCYRRHIZA GLABRA

Skin Balancing Makeup Broad Spectrum SPF 20

Active ingredients Purpose
Avobenzone 3% Sunscreen

Octinoxate 6% Sunscreen

Octisalate 4% Sunscreen

Octocrylene 2.7% Sunscreen

Uses

helps prevent sunburn

if used as directed with other sun protection measures (see Directions), decreases the risk of skin cancer and early skin aging caused by the sun

keep out of reach of children. If product is swallowed, get medical help or contact a Poison Control Center right away

Stop use and ask a doctor if rash occurs

Warnings

For external use only

Do not use on damaged or broken skin

When using this product keep out of eyes. Rinse with water to Remove.

Directions

apply liberally 15 minutes before sun exposure

use a water resistant sunscreen if swimming or sweating

reapply at least every 2 hours

children under 6 months: Ask a doctor

Sun Protection Measures

Spending time in the sun increases your risk of skin cancer and early skin aging. To decrease this risk, regularly use a sunscreen with a Broad Spectrum SPF of 15 or higher and other sun protection measures including

limit time in the sun, especially from 10 a.m. -2 p.m.

wear long-sleeve shirts, pants, hats, and sunglasses

Inactive ingredients

Water/Aqua, Diisopropyl Sebacate, Titanium Dioxide/CI 77891, Iron Oxides/CI 77491/CI77492/CI 77499, Stearic Acid, PEG-8, Cyclomethicone, Squalane, Mica, Glyceryl Stearate, PEG-100 Stearate, Triethoxycaprylylsilane, Di-PPG-3 Myristyl Ether Adipate, Polysorbate 60, Ethylhexylglycerin, Polymethyl Methacrylate, Proanediol, Caprylyl Glycol, Hexylene Glycol, Methylisothiazolinone, Cetyl Alcohol, Magnesium Aluminum Silicate, Aminomethyl Propanol, Xanthan Gum, Tocopheryl Acetate, Butylene Glycol, Magnesium, Copper, Zinc Glycopeptides, Polydodecanamideaminium Triazadiphenylethenesulfonate, Polyvinylalcohol Crosspolymer, Carica papaya Extract, Glycyrhiza Glabra (Licorice)

PACKAGE LABEL

Skin Balancing Makeup
Broad Spectrum SPF 20
30 ml 1 FL OZ